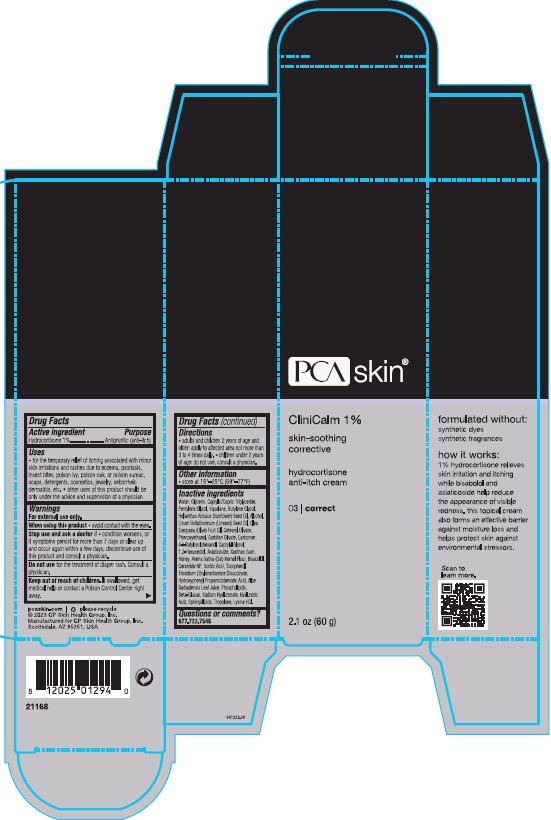 DRUG LABEL: CliniCalm
NDC: 68726-504 | Form: CREAM
Manufacturer: CP Skin Health Group, Inc.
Category: otc | Type: HUMAN OTC DRUG LABEL
Date: 20241203

ACTIVE INGREDIENTS: HYDROCORTISONE 1 g/100 g
INACTIVE INGREDIENTS: HYALURONATE SODIUM; LECITHIN, SOYBEAN; ALOE VERA LEAF; 1,2-HEXANEDIOL; 4-TERT-BUTYLCYCLOHEXANOL; ALCOHOL; ASIATICOSIDE; OATMEAL; LEVOMENOL; BUTYLENE GLYCOL; MEDIUM-CHAIN TRIGLYCERIDES; CAPRYLYL GLYCOL; CARBOMER HOMOPOLYMER, UNSPECIFIED TYPE; CERAMIDE NP; CETEARYL OLIVATE; GLYCERIN; HONEY; HYALURONIC ACID; HYDROXYPHENYL PROPAMIDOBENZOIC ACID; LINSEED OIL; LYSINE HYDROCHLORIDE; OLIVE OIL; PENTYLENE GLYCOL; PHENOXYETHANOL; SODIUM HYDROXIDE; SORBIC ACID; SORBITAN OLIVATE; SOY SPHINGOLIPIDS; SQUALANE; TOCOPHEROL; TRISODIUM ETHYLENEDIAMINE DISUCCINATE; TROPOLONE; WATER; XANTHAN GUM; YEAST .BETA.-D-GLUCAN; SUNFLOWER OIL

CliniCalm®1% Hydrocortisone Cream

Drug Facts

Active ingredient

Hydrocortisone (1%)

Purpose

Antipruritic (anti-itch)

Uses

For the temporary relief of itching and discomfort associated with minor skin irritations and rashes due to eczema, psoriasis, insect bites, poison ivy, poison oak, or poison sumac, soaps, detergents, cosmetics, jewelry, seborrheic dermatitis, etc.

Warnings

For external use only

Avoid contact with the eyes.

If condition worsens, or if symptoms persist for more than 7 days or clear up and occur again within a few days, stop use of this product and do not begin use of any other hydrocortisone product unless you have consulted a physician.

Do not use for the treatment of diaper rash. Consult a physician.

PREGNANCY OR BREAST FEEDING

If pregnant or breast-feeding, ask a health professional before use.

Keep out of reach of children. If product is swallowed, get medical help or contact a Poison Control Center right away.

Directions

Adults and children 2 years of age and older: Apply to affected area not more than 3 to 4 times daily. Children under 2 years of age: Do not use, consult a physician.

Other information

Store at 15°–25°C (59°–77°F).

Inactive ingredients

Water/Aqua/Eau, Glycerin, Caprylic/Capric Triglyceride, Alcohol Denat., Cetearyl Olivate, Squalane, Olea Europaea (Olive) Fruit Oil, Sorbitan Olivate, Caprylyl Glycol, Phenoxyethanol, Pentylene Glycol, Linum Usitatissimum (Linseed) Seed Oil, Xanthan Gum, 4-t-Butylcyclohexanol, 1,2-Hexanediol, Honey/Mel/Miel, Carbomer, Phospholipids, Asiaticoside, Beta-Glucan, Bisabolol, Lysine HCl, Sodium Hydroxide, Aloe Barbadensis Leaf Juice Powder, Ceramide NP, Sorbic Acid, Trisodium Ethylenediamine Disuccinate, Helianthus Annuus (Sunflower) Seed Oil, Butylene Glycol, Hyaluronic Acid, Sphingolipids, Tocopherol, Tropolone, Hydroxyphenyl Propamidobenzoic Acid.

Questions or comments?

877.722.7546

PRINCIPAL DISPLAY PANEL - 60 g Tube Box

PCA skin ®

CliniCalm ®1%

2.1 oz/60g